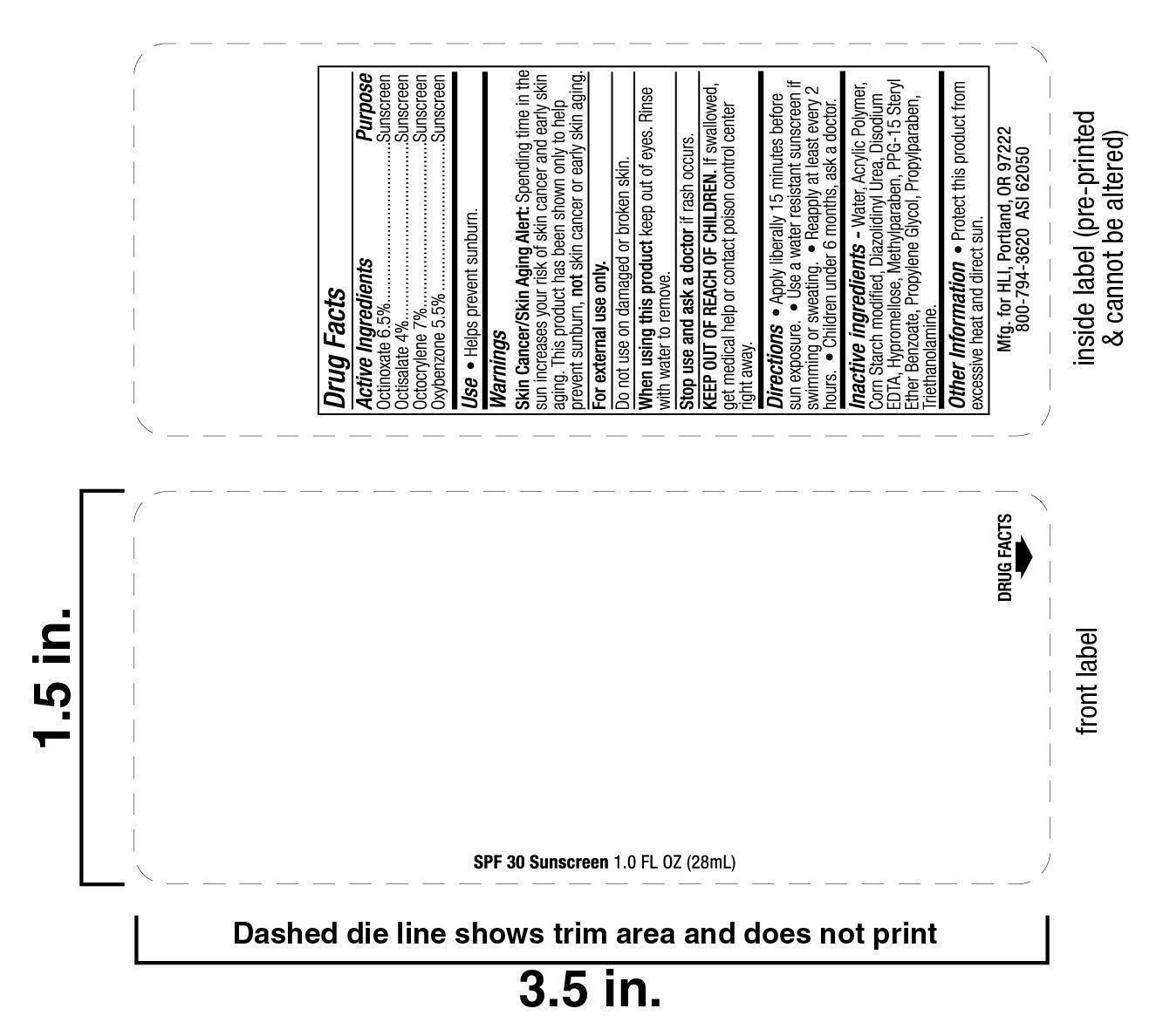 DRUG LABEL: sunscreen
NDC: 19392-400 | Form: LOTION
Manufacturer: Humphreyline
Category: otc | Type: HUMAN OTC DRUG LABEL
Date: 20120810

ACTIVE INGREDIENTS: OCTINOXATE 65 mg/1 g; OXYBENZONE 55 mg/1 g; OCTISALATE 40 mg/1 g; OCTOCRYLENE 70 mg/1 g
INACTIVE INGREDIENTS: WATER ; STARCH, CORN; TROLAMINE; HYPROMELLOSES; POLYQUATERNIUM-39 (31/40/29 ACRYLIC ACID/ACRYLAMIDE/DADMAC; 1500000 MW); PROPYLENE GLYCOL; DIAZOLIDINYL UREA    ; METHYLPARABEN; EDETATE DISODIUM    ; PROPYLPARABEN

Drug Facts

ACTIVE INGREDIENT

Octinoxate (6.5%)

Octisalate (4.0%)

Octocrylene (7.0%)

Oxybenzone (5.5%)

PURPOSE

Sunscreen

WARNINGS

For external use only.

Avoid contact with eyes.

Discontinue use if rash or irritation occurs.

Children under 6 months consult a doctor before use.

KEEP OUT OF REACH OF CHILDREN

Children under 6 months consult a doctor before use.

INDICATIONS AND USAGE

For external use only.

INACTIVE INGREDIENT

Water, PPG-15 Stearyl Ether Benzoate, Corn Starch modified, Triethanolamine, Hypromellose, Acrylic Polymer, Propylene Glycol, Diazolidinyl Urea, Methylparaben, Propylparaben, Disodium EDTA